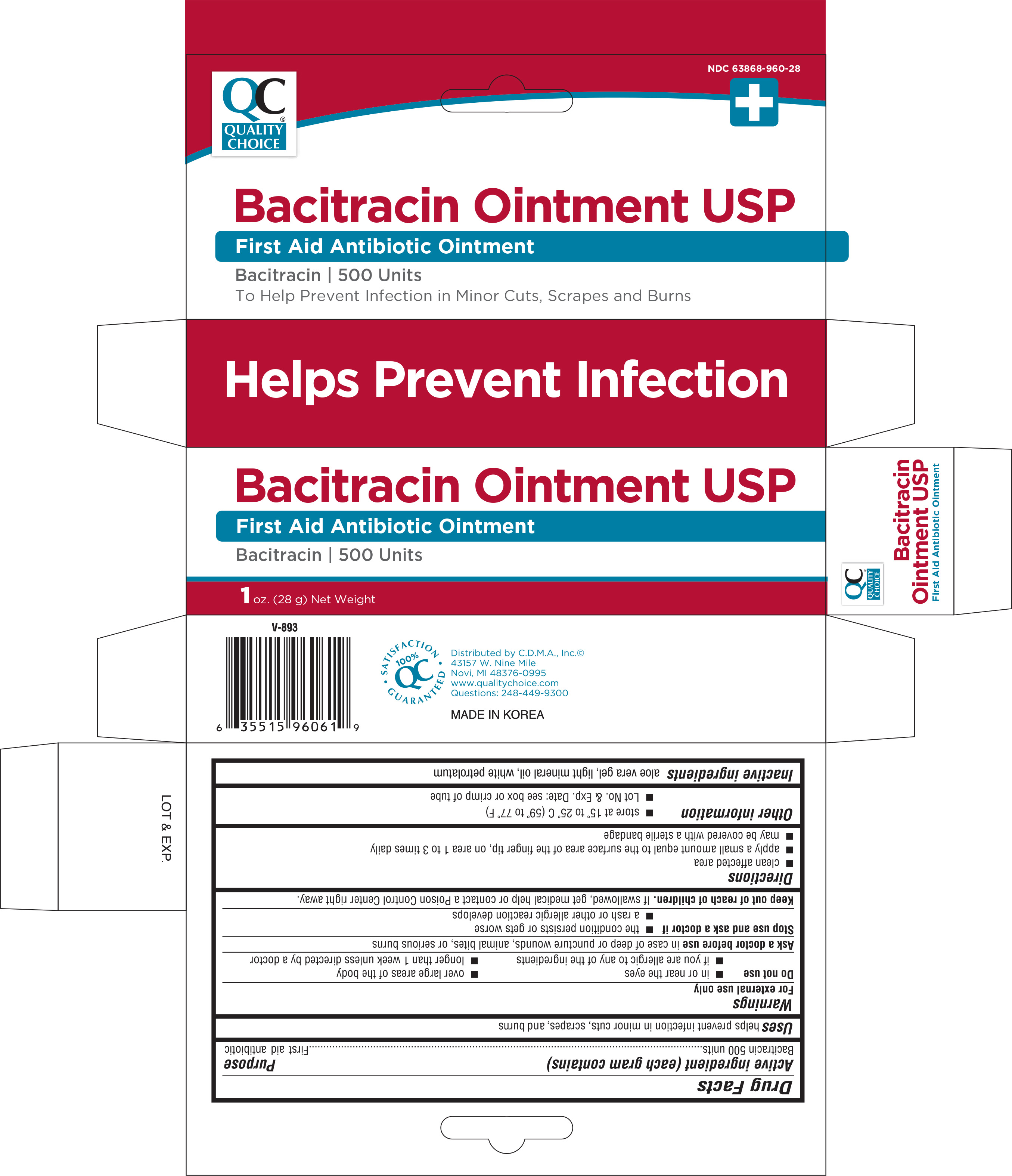 DRUG LABEL: QUALITY CHOICE BACITRACIN
NDC: 63868-960 | Form: OINTMENT
Manufacturer: CHAIN DRUG MARKETING ASSOCIATION INC
Category: otc | Type: HUMAN OTC DRUG LABEL
Date: 20161012

ACTIVE INGREDIENTS: BACITRACIN 500 [USP'U]/1 g
INACTIVE INGREDIENTS: ALOE VERA LEAF; MINERAL OIL; PETROLATUM

Active ingredients (each gram contains) Purpose

Bacitracin 500 units .......................................................................................First Aid Antibiotic

Uses

first aid to help prevent infection in

- minor cuts
- scrapes
- burns

Warnings

For external use only

Do not use

- in the eyes
- if you are allergic to any of the ingredients
- over large areas of the body
- longer than 1 week unless directed by a doctor

Ask a doctor before use in case of deep or puncture wounds, animal bites, or serious burns

Stop use and ask a doctor if

- the condition persists or gets worse
- a rash or other allergic reaction develops

Keep out of reach of children.

If swallowed, get medical help or contact a Poison Control Center right away

Directions

- clean the affected area
- apply a small amount of this product (an amount equal to the surface area of the tip of a finger) on the area 1 to 3 times daily
- may be covered with a sterile bandage

Other information

- store at 15o to 25o C (59o to 77o F)
- Lot No. and Exp. Date: see box or see crimp of tube

Inactive ingredients

aloe vera gel, light mineral oil and white petrolatum

DOSAGE AND ADMINISTRATION

DISTRIBUTED BY

C.D.M.A., Inc

NOVI, MI 48376-0995

MADE IN KOREA